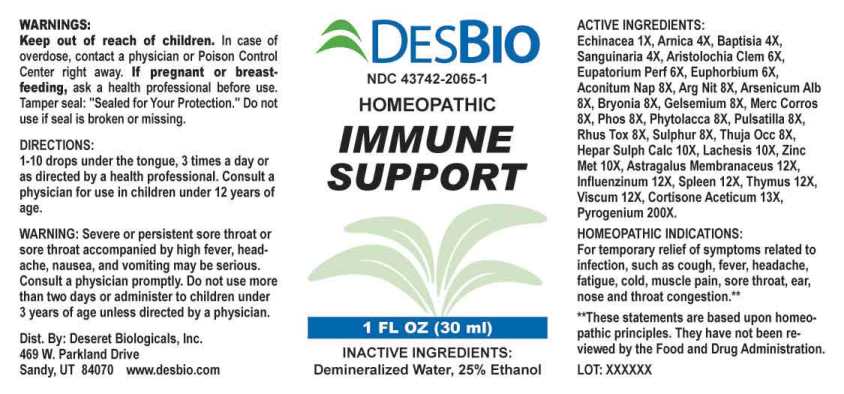 DRUG LABEL: Immune Support
NDC: 43742-2065 | Form: LIQUID
Manufacturer: Deseret Biologicals, Inc.
Category: homeopathic | Type: HUMAN OTC DRUG LABEL
Date: 20240229

ACTIVE INGREDIENTS: ECHINACEA ANGUSTIFOLIA WHOLE 1 [hp_X]/1 mL; ARNICA MONTANA WHOLE 4 [hp_X]/1 mL; BAPTISIA TINCTORIA ROOT 4 [hp_X]/1 mL; SANGUINARIA CANADENSIS ROOT 4 [hp_X]/1 mL; ARISTOLOCHIA CLEMATITIS ROOT 6 [hp_X]/1 mL; EUPATORIUM PERFOLIATUM FLOWERING TOP 6 [hp_X]/1 mL; EUPHORBIA RESINIFERA RESIN 6 [hp_X]/1 mL; ACONITUM NAPELLUS WHOLE 8 [hp_X]/1 mL; SILVER NITRATE 8 [hp_X]/1 mL; ARSENIC TRIOXIDE 8 [hp_X]/1 mL; BRYONIA ALBA ROOT 8 [hp_X]/1 mL; GELSEMIUM SEMPERVIRENS ROOT 8 [hp_X]/1 mL; MERCURIC CHLORIDE 8 [hp_X]/1 mL; PHOSPHORUS 8 [hp_X]/1 mL; PHYTOLACCA AMERICANA ROOT 8 [hp_X]/1 mL; PULSATILLA PRATENSIS WHOLE 8 [hp_X]/1 mL; TOXICODENDRON PUBESCENS LEAF 8 [hp_X]/1 mL; SULFUR 8 [hp_X]/1 mL; THUJA OCCIDENTALIS LEAFY TWIG 8 [hp_X]/1 mL; CALCIUM SULFIDE 10 [hp_X]/1 mL; LACHESIS MUTA VENOM 10 [hp_X]/1 mL; ZINC 10 [hp_X]/1 mL; ASTRAGALUS MONGHOLICUS ROOT 12 [hp_X]/1 mL; INFLUENZA A VIRUS A/VICTORIA/2570/2019 IVR-215 (H1N1) ANTIGEN (UV, FORMALDEHYDE INACTIVATED) 12 [hp_X]/1 mL; INFLUENZA A VIRUS A/DARWIN/9/2021 IVR-228 (H3N2) ANTIGEN (UV, FORMALDEHYDE INACTIVATED) 12 [hp_X]/1 mL; INFLUENZA B VIRUS B/AUSTRIA/1359417/2021 BVR-26 ANTIGEN (UV, FORMALDEHYDE INACTIVATED) 12 [hp_X]/1 mL; INFLUENZA B VIRUS B/PHUKET/3073/2013 ANTIGEN (UV, FORMALDEHYDE INACTIVATED) 12 [hp_X]/1 mL; SUS SCROFA SPLEEN 12 [hp_X]/1 mL; SUS SCROFA THYMUS 12 [hp_X]/1 mL; VISCUM ALBUM FRUITING TOP 12 [hp_X]/1 mL; CORTISONE ACETATE 13 [hp_X]/1 mL; RANCID BEEF 200 [hp_X]/1 mL
INACTIVE INGREDIENTS: WATER; ALCOHOL

DRUG FACTS:

ACTIVE INGREDIENTS:

Echinacea (Angustifolia) 1X, Arnica Montana 4X, Baptisia Tinctoria 4X, Sanguinaria Canadensis 4X, Aristolochia Clematitis 6X, Eupatorium Perfoliatum 6X, Euphorbium Officinarum 6X, Aconitum Napellus 8X, Argentum Nitricum 8X, Arsenicum Album 8X, Bryonia (Alba) 8X, Gelsemium Sempervirens 8X, Mercurius Corrosivus 8X, Phosphorus 8X, Phytolacca Decandra 8X, Pulsatilla (Pratensis) 8X, Rhus Tox 8X, Sulphur 8X, Thuja Occidentalis 8X, Hepar Sulphuris Calcareum 10X, Lachesis Mutus 10X, Zincum Metallicum 10X, Astragalus Membranaceus 12X, Influenzinum (2022-2023) 12X, Spleen (Suis) 12X, Thymus (Suis) 12X, Viscum Album 12X,

PURPOSES:

For temporary relief of symptoms related to infection, such as cough, fever, headache, fatigue, cold, muscle pain, sore throat, ear, nose and throat congestion.**

**These statements are based upon homeopathic principles. They have not been reviewed by the Food and Drug Administration.

USES:

For temporary relief of symptoms related to infection, such as cough, fever, headache, fatigue, cold, muscle pain, sore throat, ear, nose and throat congestion.**

**These statements are based upon homeopathic principles. They have not been reviewed by the Food and Drug Administration.

WARNINGS:

Keep out of reach of children. In case of overdose, contact a physician or Poison Control Center right away.

If pregnant or breast-feeding, ask a health professional before use.

Tamper seal: "Sealed for Your Protection." Do not use if seal is broken or missing.

WARNING: Severe or persistent sore throat or sore throat accompanied by high fever, headache, nausea, and vomiting may be serious. Consult a physician promptly. Do not use more than two days or administer to children under 3 years of age unless directed by a physician.

Keep out of reach of children. In case of overdose, contact a physician or Poison Control Center right away.

DIRECTIONS:

1-10 drops under the tongue, 3 times a day or as directed by a health professional. Consult a physician for use in children under 12 years of age.

INACTIVE INGREDIENTS:

Demineralized Water, 25% Ethanol

QUESTIONS:

Dist. By: Deseret Biologicals, Inc.
469 W. Parkland Drive
Sandy, UT 84070 www.desbio.com

PACKAGE LABEL DISPLAY:

DESBIO
NDC 43742-2065-1
HOMEOPATHIC
IMMUME
SUPPORT
1 FL OZ (30 ml)